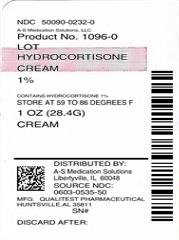 DRUG LABEL: Hydrocortisone
NDC: 50090-0232 | Form: CREAM
Manufacturer: A-S Medication Solutions
Category: otc | Type: HUMAN OTC DRUG LABEL
Date: 20170925

ACTIVE INGREDIENTS: HYDROCORTISONE 10 mg/1 g
INACTIVE INGREDIENTS: CETYL ALCOHOL; DIAZOLIDINYL UREA; ISOPROPYL PALMITATE; MINERAL OIL; LANOLIN ALCOHOLS; POLYSORBATE 40; PROPYLENE GLYCOL; PROPYLENE GLYCOL MONOSTEARATE; WATER; SORBIC ACID; SORBITAN MONOPALMITATE; STEARYL ALCOHOL; XANTHAN GUM

Hydrocortisone Maximum Strength

Active ingredient

Hydrocortisone 1.0%

Purpose

Anti-itch

Uses

for the temporary relief of itching associated with minor skin irritations, inflammation and rashes due to:

- cosmetics
- soaps
- jewelry
- insect bites
- psoriasis
- eczema
- detergents
- seborrheic dermatitis
- external genital and anal itching
- poison ivy, poison oak, or poison sumac

Other uses of this product should be only under the advice and supervision of a doctor.

Do not use

- for the treatment of diaper rash. Consult a doctor.
- for external genital itching if you have vaginal discharge. Consult a doctor.

When using this product

- avoid contact with eyes
- do not use more than directed unless told to do so by a doctor
- do not put directly into the rectum by using fingers or any mechanical device or applicator

Stop use and ask a doctor if

- condition worsens, symptoms persist for more than 7 days or clear up and occur again within a few days, and do not begin use of any other hydrocortisone product unless you have asked a doctor
- rectal bleeding occurs

Keep out of reach of children.

If swallowed, get medical help or contact a Poison Control Center immediately.

Directions

Adults and children 2 years of age and older

- apply to affected area not more than 3 to 4 times daily

Children under 2 years of age

- do not use. Consult a doctor.

For external anal itching

- adults: when practical, cleanse the affected area with mild soap and warm water and rinse thoroughly or by patting or blotting with toilet tissue or a soft cloth before application of this product
- children under 12 years of age with external anal itching: consult a doctor

Other information

- store at 15° to 30°C (59° to 86°F)
- lot number and expiration date: See crimp of tube or box

You may report serious side effects to: 130 Vintage Drive, Huntsville, AL 35811.

Inactive ingredients

cetyl alcohol, diazolidinyl urea, isopropyl palmitate, mineral oil/lanolin alcohol, polysorbate 40, propylene glycol, propylene glycol monostearate, purified water, sorbic acid, sorbitan monopalmitate, stearyl alcohol, xanthan gum

Made in the USA
for Qualitest Pharmaceuticals
Huntsville, AL 35811

Rev. 5/15 R6
8265556 0534

HOW SUPPLIED

Product: 50090-0232

NDC: 50090-0232-0 28.4 g in a TUBE